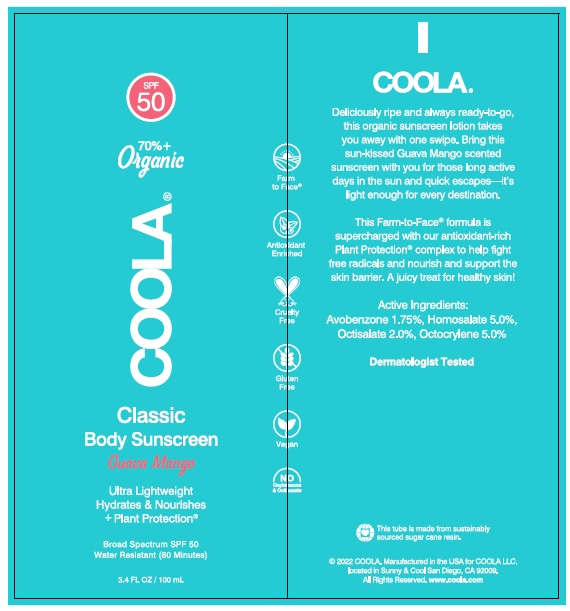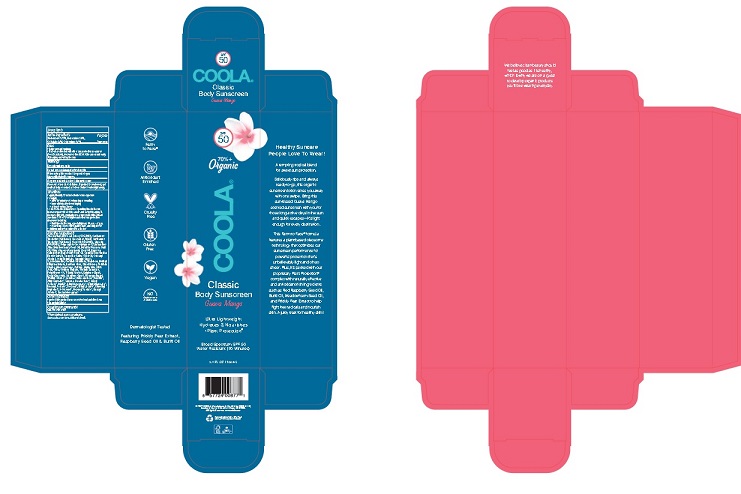 DRUG LABEL: COOLA CLASSIC BODY SUNSCREEN Guava Mango Broad Spectrum
NDC: 79753-075 | Form: LOTION
Manufacturer: COOLA LLC
Category: otc | Type: HUMAN OTC DRUG LABEL
Date: 20241227

ACTIVE INGREDIENTS: AVOBENZONE 1.75 g/100 mL; HOMOSALATE 5.0 g/100 mL; OCTISALATE 2.0 g/100 mL; OCTOCRYLENE 5.0 g/100 mL
INACTIVE INGREDIENTS: ALOE VERA LEAF; BRASSICA RAPA SUBSP. OLEIFERA OIL; BUTYLENE GLYCOL; CAMELINA SATIVA SEED OIL; CAPRYLYL GLYCOL; CARTHAMUS TINCTORIUS SEED OLEOSOMES; SAFFLOWER OIL; CETOSTEARYL ALCOHOL; CETYL PALMITATE; DECYL GLUCOSIDE; DIMETHICONE; GLYCERIN; 1,2-HEXANEDIOL; MEADOWFOAM SEED OIL; MAURITIA FLEXUOSA FRUIT OIL; METHYL DIHYDROABIETATE; OPUNTIA FICUS-INDICA FLOWER; AMMONIUM ACRYLOYLDIMETHYLTAURATE, DIMETHYLACRYLAMIDE, LAURYL METHACRYLATE AND LAURETH-4 METHACRYLATE COPOLYMER, TRIMETHYLOLPROPANE TRIACRYLATE CROSSLINKED (45000 MPA.S); DIMETHICONE/VINYL DIMETHICONE CROSSPOLYMER (SOFT PARTICLE); RASPBERRY SEED OIL; SILICON DIOXIDE; SODIUM HYDROXIDE; PHYTATE SODIUM; SORBITAN MONOOLEATE; SORBITAN MONOPALMITATE; TROPOLONE; WATER; XANTHAN GUM

COOLA CLASSIC BODY SUNSCREEN Guava Mango Broad Spectrum SPF 50

DRUG FACTS

Active Ingredients
Avobenzone 1.75% Homosalate 5.0%
Octisalate 2.0% Octocrylene 5.0%

Purpose
Sunscreen

Uses
• helps prevent sunburn
• if used as directed with other sun protection measures
(see Directions) decreases the risk of skin cancer and
early skin aging caused by the sun.

Warnings
For external use only.

Do not use on damaged or broken skin.

When using this product keep out of eyes.
Rinse with water to remove.

Stop use and ask doctor if rash occurs.

Keep out of reach of children. If product is swallowed
get medical help or contact a Poison Control Center right away.

Directions
• apply liberally 15 minutes before sun exposure
• reapply:
• after 80 minutes of swimming or sweating
• immediately after towel drying
• at least every 2 hours
• Sun Protection Measures. Spending time in the sun
increases your risk of skin cancer and early skin aging. To
decrease this risk, regularly use a sunscreen with a broad
spectrum SPF of 15 or higher and after sun protection.
measures including:
• limit time in the sun, especially from 10 a.m. – 2 p.m.
• wear long-sleeve shirts, pants, hats, and sunglasses.
• Children under 6 months: Ask a doctor

Inactive Ingredients
Aloe Barbadensis Leaf Juice (ORGANIC), Brassica
Campestris (Rapeseed) Seed Oil, Butylene Glycol,
Camelina Sativa Seed Oil, Caprylyl Glycol, Carthamus
Tinctorius (Safflower) Oleosomes, Carthamus
Tinctorius (Safflower) Seed Oil (ORGANIC), Cetearyl
Alcohol, Cetyl Palmitate, Decyl Glucoside, Dimethicone,
Flavor*, Glycerin (ORGANIC), 1,2-Hexanediol,
Limnanthes Alba (Meadowfoam) Seed Oil, Mauritia
Flexuosa (Buriti) Fruit Oil, Methyl Dihydroabietate,
Opuntia Ficus-Indica Flower Extract, Polyacrylate
Crosspolymer-6, Polysilicone-11, Rubus Idaeus
(Raspberry) Seed Oil, Silica, Sodium Hydroxide, Sodium
Phytate, Sorbitan Oleate, Sorbitan Palmitate, Tropolone,
Water, Xanthan Gum

Other Information

- protect this product from excessive heat and direct sun
- may stain fabrics

Questions or Comments? Call 760-940-2125

Package Label

SPF
50

70% +
Organic

COOLA

Classic
Body Sunscreen
Guava Mango

Ultra Lightweight
Hydrates & Nourishes
+Plant Protection®

Broad Spectrum SPF 50
Water Resistant (80 Minutes)

3.4 FL OZ / 100 mL

2020 COOLA. Distributed by: COOLA LLC,

located in Sunny& Cool San Diego, CA 92009.

All Rights Reserved. ww.coola.com

Box

Tube

res